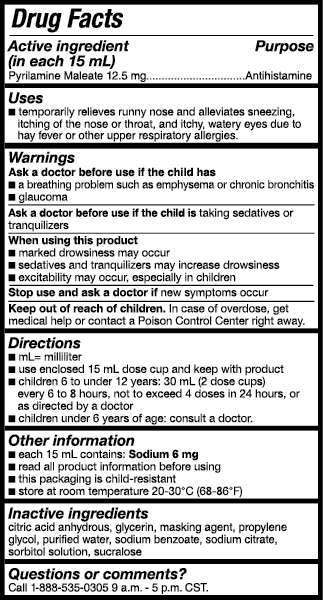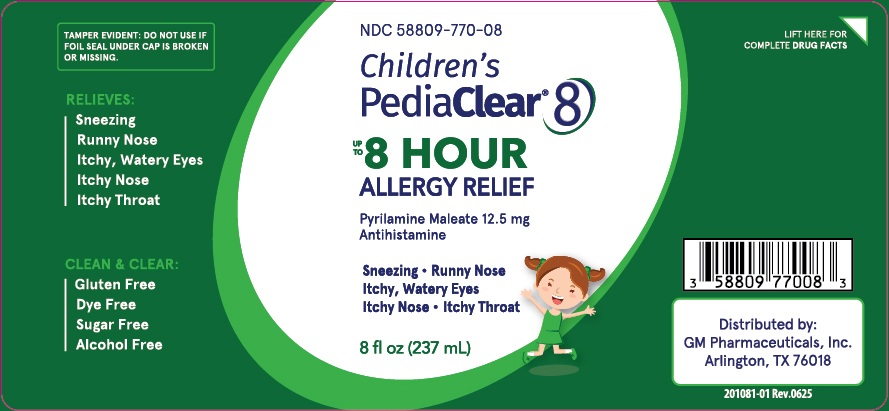 DRUG LABEL: Childrens PediaClear 8
NDC: 58809-770 | Form: LIQUID
Manufacturer: GM Pharmaceuticals, INC
Category: otc | Type: HUMAN OTC DRUG LABEL
Date: 20251003

ACTIVE INGREDIENTS: PYRILAMINE MALEATE 12.5 mg/15 mL
INACTIVE INGREDIENTS: ANHYDROUS CITRIC ACID; GLYCERIN; PROPYLENE GLYCOL; WATER; SODIUM BENZOATE; SODIUM CITRATE; SORBITOL; SUCRALOSE

Childrens PediaClear 8

CHILDRENS PEDIACLEAR 8

NDC: 58809-770-08

Active ingredients

(in each 15 mL)

Pyrilamine Maleate 12.5 mg

Purpose

Antihistamine

Uses

■ temporarily relieves runny nose and alleviates sneezing, itching of the nose or throat, and itchy, watery eyes due to hay fever or other upper respiratory allergies.

Warnings

Ask a doctor before use if the child has

■ a breathing problem such as emphysema or chronic bronchitis

■ glaucoma

Ask a doctor before use if the child is

taking sedatives or tranquilizers

When using this product

■ marked drowsiness may occur

■ sedatives and tranquilizers may increase drowsiness

■ excitability may occur, especially in children

Stop use and ask a doctor if

new symptoms occur

Keep out of reach of children.

In case of overdose, get medical help or contact a Poison Control Center right away.

Directions

■ mL= milliliter
■ use enclosed 15 mL dose cup and keep with product
■ children 6 to under 12 years: 30 mL (2 dose cups) every 6 to 8 hours, not to exceed 4 doses in 24 hours, or as directed by a doctor
■ children under 6 years of age: consult a doctor.

Other information

■ each 15 mL contains: Sodium 6 mg
■ read all product information before using
■ this packaging is child-resistant
■ store at room temperature 20-30°C (68-86°F)

Inactive ingredients

citric acid anhydrous, glycerin, propylene glycol, purified water, sodium benzoate, sodium citrate, sorbitol, sucralose

Questions or comments?

Call 1-888-535-0305 9 a.m. - 5 p.m. CST.

PRINCIPAL DISPLAY PANEL

NDC 58809-770-08
Children’s
PediaClear
8 Eight
8 fl oz (237 mL)